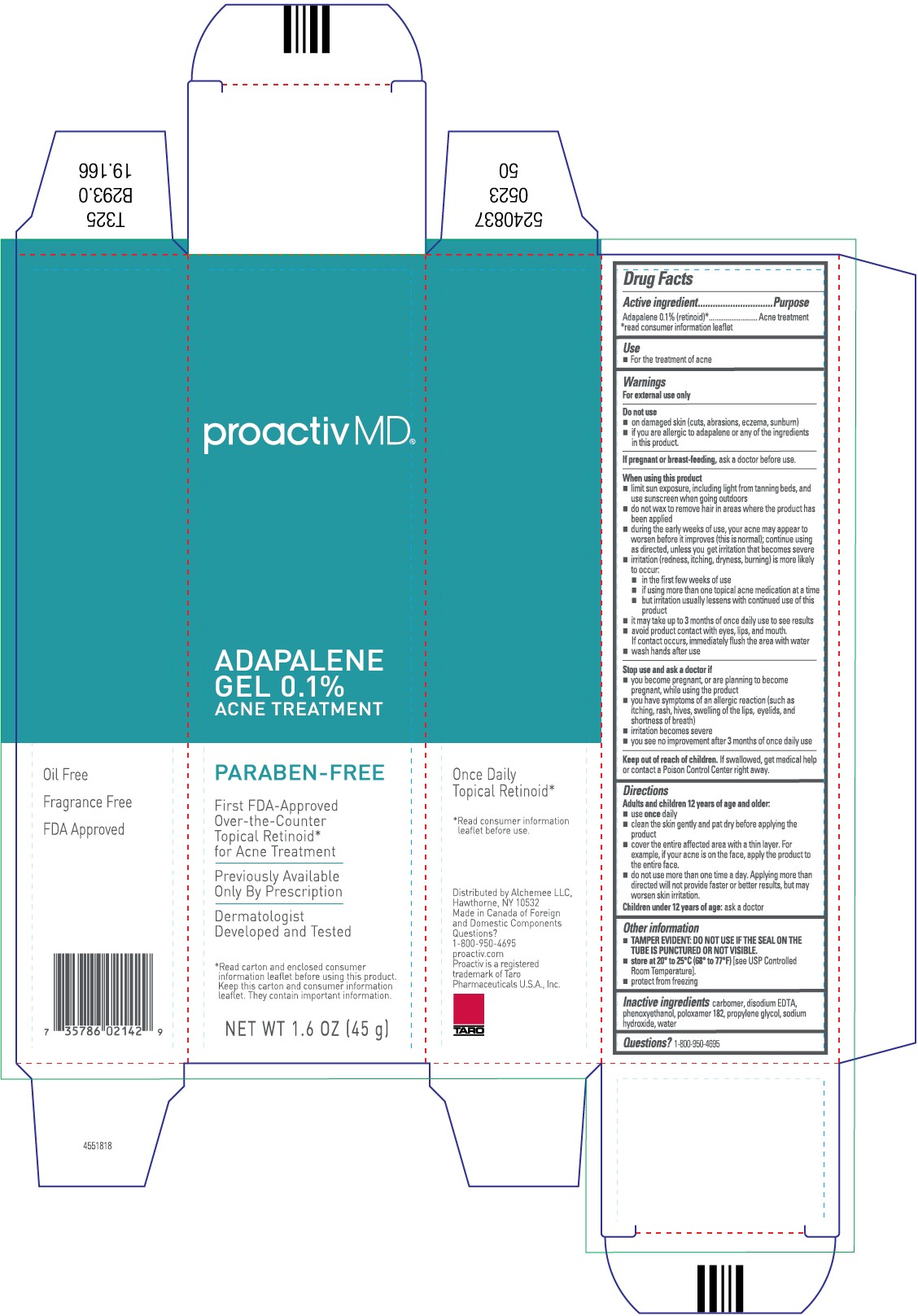 DRUG LABEL: Proactiv MD Adapalene
NDC: 11410-958 | Form: GEL
Manufacturer: Alchemee, LLC
Category: otc | Type: HUMAN OTC DRUG LABEL
Date: 20260107

ACTIVE INGREDIENTS: ADAPALENE 0.1 g/100 g
INACTIVE INGREDIENTS: CARBOMER HOMOPOLYMER TYPE C (ALLYL PENTAERYTHRITOL CROSSLINKED); EDETATE DISODIUM; POLOXAMER 182; PROPYLENE GLYCOL; WATER; SODIUM HYDROXIDE; PHENOXYETHANOL

Proactiv MD®Adapalene Gel 0.1%
Acne Treatment

Drug Facts

Active ingredient

Adapalene 0.1% (retinoid) [read consumer information leaflet]

Purpose

Acne treatment

Use

- For the treatment of acne

Warnings

For external use only

Do not use

- on damaged skin (cuts, abrasions, eczema, sunburn)
- if you are allergic to adapalene or any of the ingredients in this product.

PREGNANCY OR BREAST FEEDING

If pregnant or breast-feeding, ask a doctor before use.

When using this product

- limit sun exposure, including light from tanning beds, and use sunscreen when going outdoors
- do not wax to remove hair in areas where the product has been applied
- during the early weeks of use, your acne may appear to worsen before it improves (this is normal); continue using as directed, unless you get irritation that becomes severe
- irritation (redness, itching, dryness, burning) is more likely to occur:
  - in the first few weeks of use
  - if using more than one topical acne medication at a time
  - but irritation usually lessens with continued use of this product
- it may take up to 3 months of once daily use to see results
- avoid product contact with eyes, lips, and mouth. If contact occurs, immediately flush the area with water.
- wash hands after use

Stop use and ask a doctor if

- you become pregnant, or are planning to become pregnant, while using the product
- you have symptoms of an allergic reaction (such as itching, rash, hives, swelling of the lips, eyelids, and shortness of breath)
- irritation becomes severe
- you see no improvement after 3 months of once daily use

Keep out of reach of children. If swallowed, get medical help or contact a Poison Control Center right away.

Directions

Adults and children 12 years of age and older:

- use once daily
- clean the skin gently and pat dry before applying the product
- cover the entire affected area with a thin layer. For example, if your acne is on the face, apply the product to the entire face.
- do not use more than one time a day. Applying more than directed will not provide faster or better results, but may worsen skin irritation.

Children under 12 years of age: ask a doctor

Other information

- TAMPER EVIDENTl DONOT USE IF THE SEAL ON THE TUBE IS PUNCTURED OR VISIBLE.
- store at 20° to 25°C (68°- 77°F) (see USP Controlled Room Temperature).
- protect from freezing

Inactive ingredients

carbomer, disodium EDTA, phenoxyethanol, poloxamer 182, propylene glycol, sodium hydrixide, water

Distributed by Alchemee LLC,
Hawthorne, NY 10532

Made in Canada of Foreign

and Domestic Components

Questions?

1-800-950-4695

PRINCIPAL DISPLAY PANEL - 45 g Tube Box

proactivMD®

ADAPALENE GEL 0.1%
ACNE TREATMENT

PARABEN-FREE

First FDA-Approved
Over-the-Counter
Topical Retinoid* for
Acne Treatment

Previously Available
Only By Prescription

Dermatologist
Developed and Tested

*Read carton and enclosed consumer
information leaflet before using
this product. Keep this carton and
consumer information leaflet.
They contain important information.

NET WT 1.6 OZ (45 g)